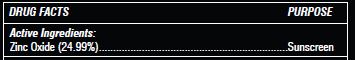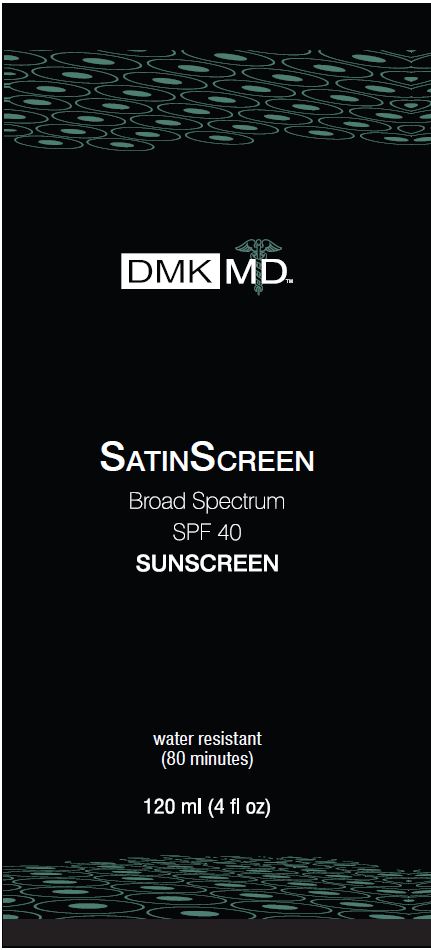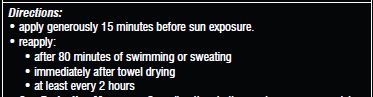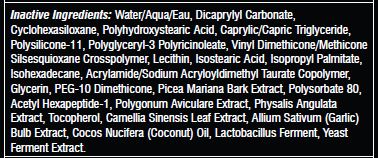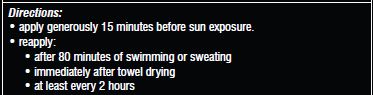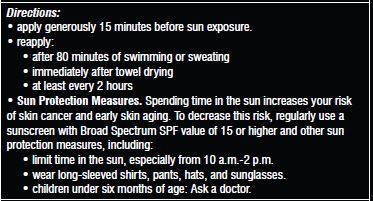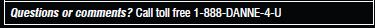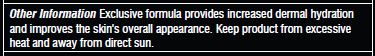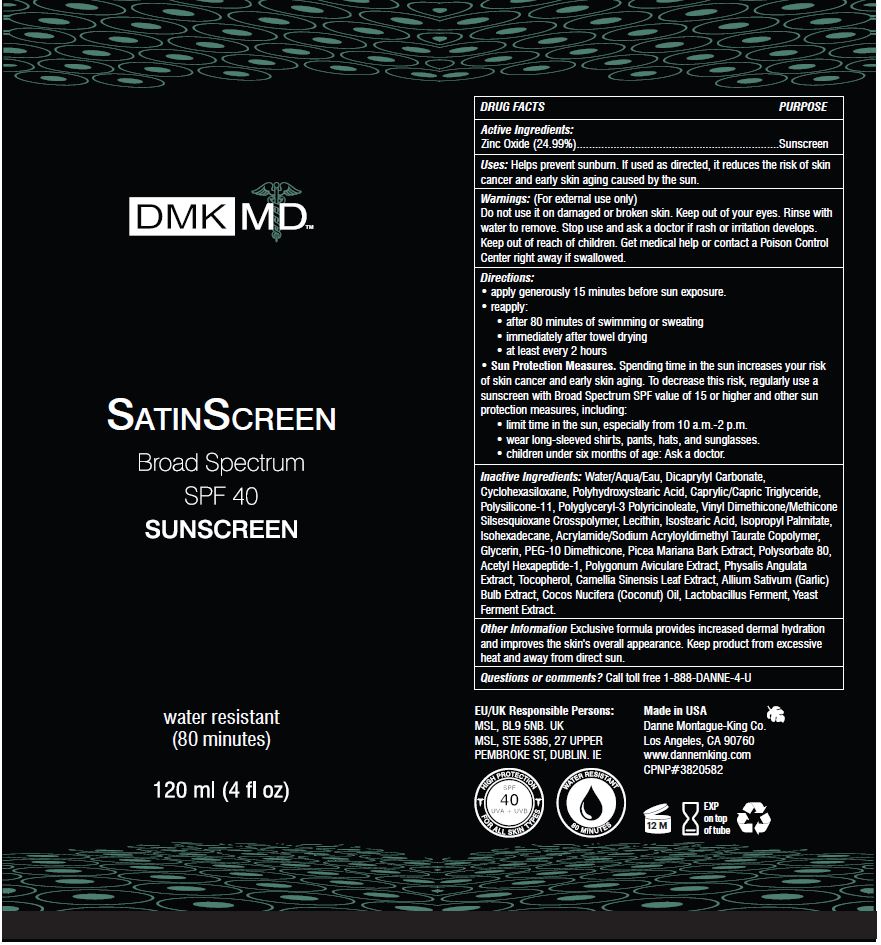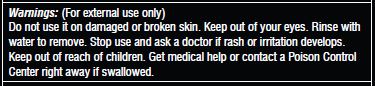 DRUG LABEL: DMK MD Satinscreen
NDC: 81537-106 | Form: LOTION
Manufacturer: Danne Montague King
Category: otc | Type: HUMAN OTC DRUG LABEL
Date: 20240719

ACTIVE INGREDIENTS: ZINC OXIDE 24.99 g/100 mL
INACTIVE INGREDIENTS: GREEN TEA LEAF 0.7 g/100 mL; CYCLOMETHICONE 6 10 g/100 mL; POLYGLYCERYL-3 RICINOLEATE 2.142 g/100 mL; COCONUT OIL 0.3 g/100 mL; DIMETHICONE/VINYL DIMETHICONE CROSSPOLYMER (SOFT PARTICLE) 3.5 g/100 mL; SODIUM ACRYLOYLDIMETHYLTAURATE-ACRYLAMIDE COPOLYMER (1:1; 90000-150000 MPA.S) 0.569 g/100 mL; YEAST, UNSPECIFIED 0.2 g/100 mL; GARLIC 0.3 g/100 mL; POLYSORBATE 80 0.142 g/100 mL; ISOHEXADECANE 0.712 g/100 mL; PEG-10 DIMETHICONE (600 CST) 0.355 g/100 mL; WATER 30.26 g/100 mL; ISOSTEARIC ACID 1.071 g/100 mL; GLYCERIN 0.525 g/100 mL; ACETYL HEXAPEPTIDE-1 0.025 g/100 mL; POLYGONUM AVICULARE WHOLE 0.02 g/100 mL; VINYL DIMETHICONE/METHICONE SILSESQUIOXANE CROSSPOLYMER 0.5 g/100 mL; ISOPROPYL PALMITATE 0.85 g/100 mL; MEDIUM-CHAIN TRIGLYCERIDES 3.927 g/100 mL; PHYSALIS ANGULATA 0.28 g/100 mL; DICAPRYLYL CARBONATE 10.098 g/100 mL; TOCOPHEROL 0.2 g/100 mL; POLYHYDROXYSTEARIC ACID (2300 MW) 6.663 g/100 mL; LECITHIN, SOYBEAN 1.121 g/100 mL

DMK MD Satinscreen SPF 40